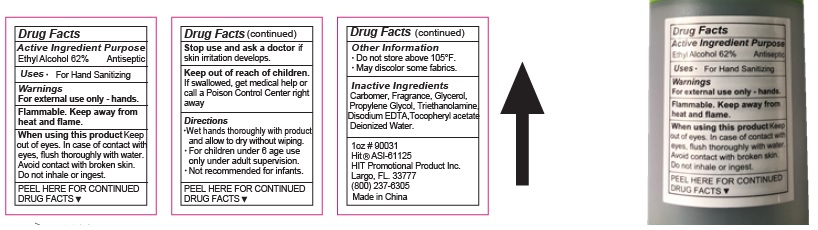 DRUG LABEL: HAND SANITIZER
NDC: 75613-020 | Form: GEL
Manufacturer: Ningbo Lanzi Cosmetic Technology Co., Ltd
Category: otc | Type: HUMAN OTC DRUG LABEL
Date: 20211111

ACTIVE INGREDIENTS: ALCOHOL 62 mL/100 mL
INACTIVE INGREDIENTS: WATER; PROPYLENE GLYCOL; EDETATE DISODIUM; TROLAMINE; .ALPHA.-TOCOPHEROL ACETATE, D-; GLYCERIN

HAND SANITIZER

Active ingredient

Ethyl Alcohol 62%

Purpose

Antiseptic

Use

For hand sanitizing

Warnings

For external use only.

Flammable. Keep product away from heat or flame.

When using this product keep out of eyes. In case of contact with eyes, flush thoroughly with water. Avoid contact with broken skin.

Do not inhale or ingest.

Stop use and ask a doctor if skin irritation develops.

Keep out of reach of children.

If swallowed, get medical help or call a Poison Control Center right away.

Directions

- Wet hands thoroughly with product and allow to dry without wiping.
- For children under 6 age use only under adult supervision.
- Not recommended for infants.

Inactive ingredients

Carbomer, Fragrance, Glycerol, Propylene Glycol, Triethanolamine, Disodium Edta, Tocopheryl Acetate, Deionized Water